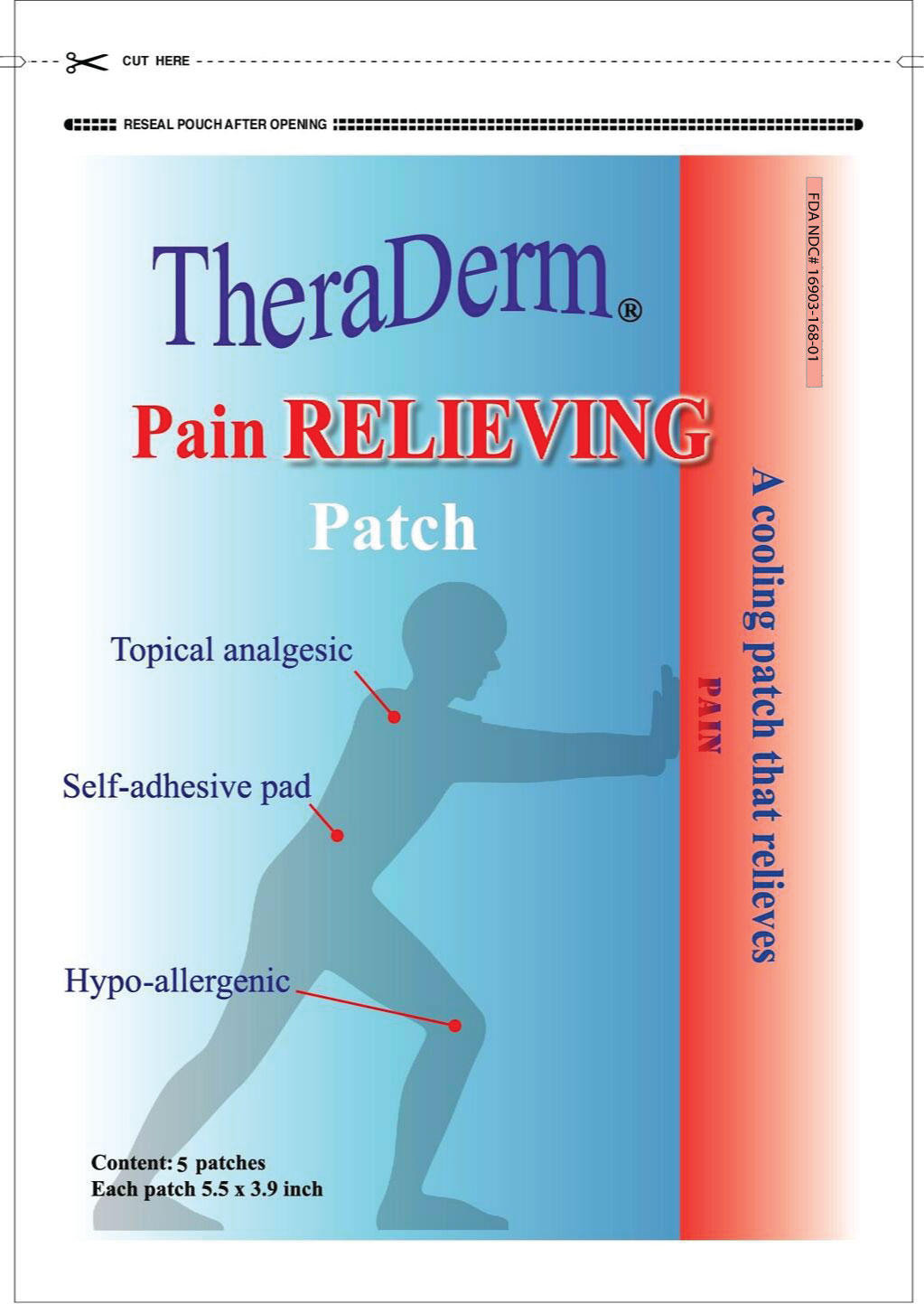 DRUG LABEL: Theraderm Pain Relieving Patch
NDC: 16903-168 | Form: PATCH
Manufacturer: Manna Omni International Incorporated
Category: otc | Type: HUMAN OTC DRUG LABEL
Date: 20171109

ACTIVE INGREDIENTS: MENTHOL 105 1/1 1; METHYL SALICYLATE 31.5 1/1 1; EUCALYPTUS OIL 105 1/1 1
INACTIVE INGREDIENTS: ALOE 105 1/1 1

TheraDerm Pain Relieving Patch

Drug Facts: Active Ingredients

Menthol

Methal Salicylate

Eucalyptus Oil

Uses:

Temporarily relieves minor aches and pains of muscles and joints due to simple back ache, arthritis, strains, and sprains.

Warnings: For External Use Only

Use as directed

do not get into eyes or on mucous membranes

do not apply to wounds, damaged. or sensative skin

do not bangage tightly or cover with any type of wrap or cloth

do not use with a heating pad or apply external heat

do not use in combination with other external analgesic products

Stop use and ask a doctor if:

Condition worsens

excessive redness, burning,irritation, or discomfort of the skin developes

pain persists for more than seven days

symptoms clear up and occur again within a few days

Keep out of the Reach of Children

If swallowed, get medical help and contact a poision center right away.

Directions:

Adults and children 12 years and over apply to affected area, change patch 2 to 3 times daily.

Children under 12 years ask a doctor before use.

How to apply:

Clean and dry affected area.

Cut open poutch and remove patch.

If desired, cut patch to size.

remove protective film from adhesive, apply directly onto site of pain, and secure ith adhesive strips.

Inactive Ingredients

Aloe extract, Zinc Oxide, Angelicae Sinensis RX, Cauda, Salviae Militorrhiza. CHuanxiong, Paeonea Rubra, Frankinsence, Myrrha, Notoginseng, Carthami Flos Persicae Sm, Angelica Pubescentis RX, Zingiberis RZ, Thymol.

Indications and Usage:

Thera Derm Pain relieving Patch is used for minor back aches, muscle aches, sprains, and strains.